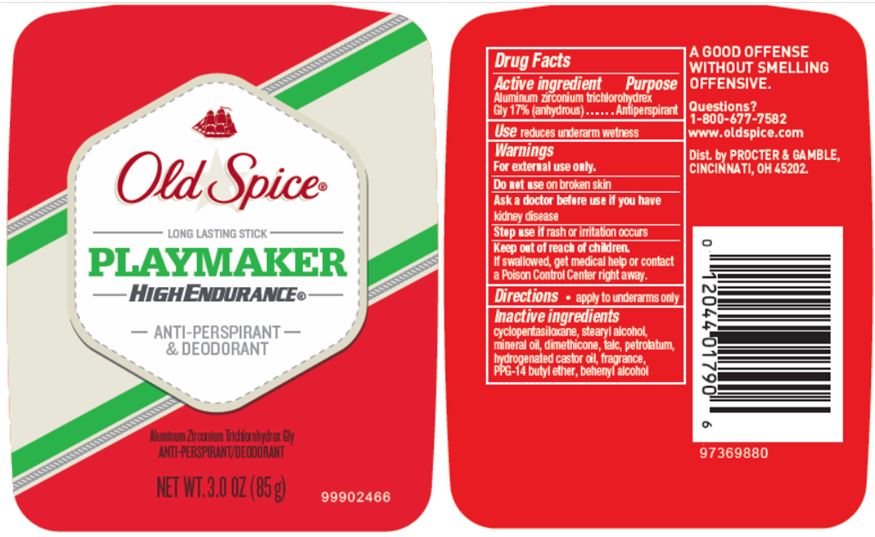 DRUG LABEL: Old Spice Playmaker
NDC: 69423-597 | Form: STICK
Manufacturer: The Procter & Gamble Manufacturing Company
Category: otc | Type: HUMAN OTC DRUG LABEL
Date: 20251218

ACTIVE INGREDIENTS: ALUMINUM ZIRCONIUM PENTACHLOROHYDREX GLY 17 g/100 g
INACTIVE INGREDIENTS: CYCLOMETHICONE 5; STEARYL ALCOHOL; PPG-14 BUTYL ETHER; HYDROGENATED CASTOR OIL; PETROLATUM; MINERAL OIL; DOCOSANOL; DIMETHICONE

Old Spice® Playmaker
High Endurance®

Drug Facts

Active ingredient

Aluminum zirconium pentachlorohydrex Gly 17% (anhydrous)

Purpose

Antiperspirant

Use

reduces underarm wetness

Warnings

For external use only.

Do not use on broken skin

Ask a doctor before use if you have kidney disease

Stop use if rash or irritation occurs

Keep out of reach of children. If swallowed, get medical help or contact a Poison Control Center right away.

Directions

- apply to underarms only

Inactive ingredients

cyclopentasiloxane, stearyl alcohol, mineral oil, dimethicone, petrolatum, hydrogenated castor oil, fragrance, PPG-14 butyl ether, behenyl alcohol

Questions?

1-800-677-7582

Dist. by PROCTER & GAMBLE, CINCINNATI, OH 45202.

PRINCIPAL DISPLAY PANEL - 85 g Canister Label

Old Spice®

LONG LASTING STICK
PLAYMAKER
HIGH ENDURANCE®

ANTI-PERSPIRANT
& DEODORANT

Aluminum Zirconium Trichlorohydrex Gly
ANTI-PERSPIRANT/DEODORANT

NET WT. 3.0 OZ (85 g)